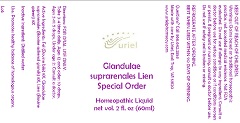 DRUG LABEL: Glandulae suprarenales Lien Special Order
NDC: 48951-5091 | Form: LIQUID
Manufacturer: Uriel Pharmacy Inc.
Category: homeopathic | Type: HUMAN OTC DRUG LABEL
Date: 20181130

ACTIVE INGREDIENTS: BOS TAURUS BILE 8 [hp_X]/1 mL; BOS TAURUS ADRENAL GLAND 8 [hp_X]/1 mL; BOS TAURUS SPLEEN 8 [hp_X]/1 mL
INACTIVE INGREDIENTS: WATER

Glandulae suprarenales Lien Special Order

INDICATIONS AND USAGE

Directions: FOR ORAL USE ONLY.

DOSAGE AND ADMINISTRATION

Take 3-4 times daily. Ages 12 and older: 10 drops. Ages 2-11: 5 drops. Under age 2: Consult a doctor.

ACTIVE INGREDIENT

Active Ingredients: Fel (Bovine bile) 8X, Glandulae suprarenales (Bovine adrenal glands) 8X, Lien (Bovine spleen) 8X

Inactive Ingredient: Distilled water

PURPOSE

Use: Promotes healthy balance of homologous organs.

KEEP OUT OF REACH OF CHILDREN.

WARNINGS

Warnings: Claims based on traditional homeopathic practice, not accepted medical evidence. Not FDA evaluated. Do not use if allergic to any ingredient. Consult a doctor before use for serious conditions or if conditions worsen or persist. If pregnant or nursing, consult a doctor before use. Do not use if safety seal is broken or missing.

REFRIGERATE AFTER OPENING.
BEST WHEN USED WITHIN 90 DAYS OF OPENING.

Questions? Call 866.642.2858
Made with care by Uriel, East Troy, WI 53120
www.urielpharmacy.com